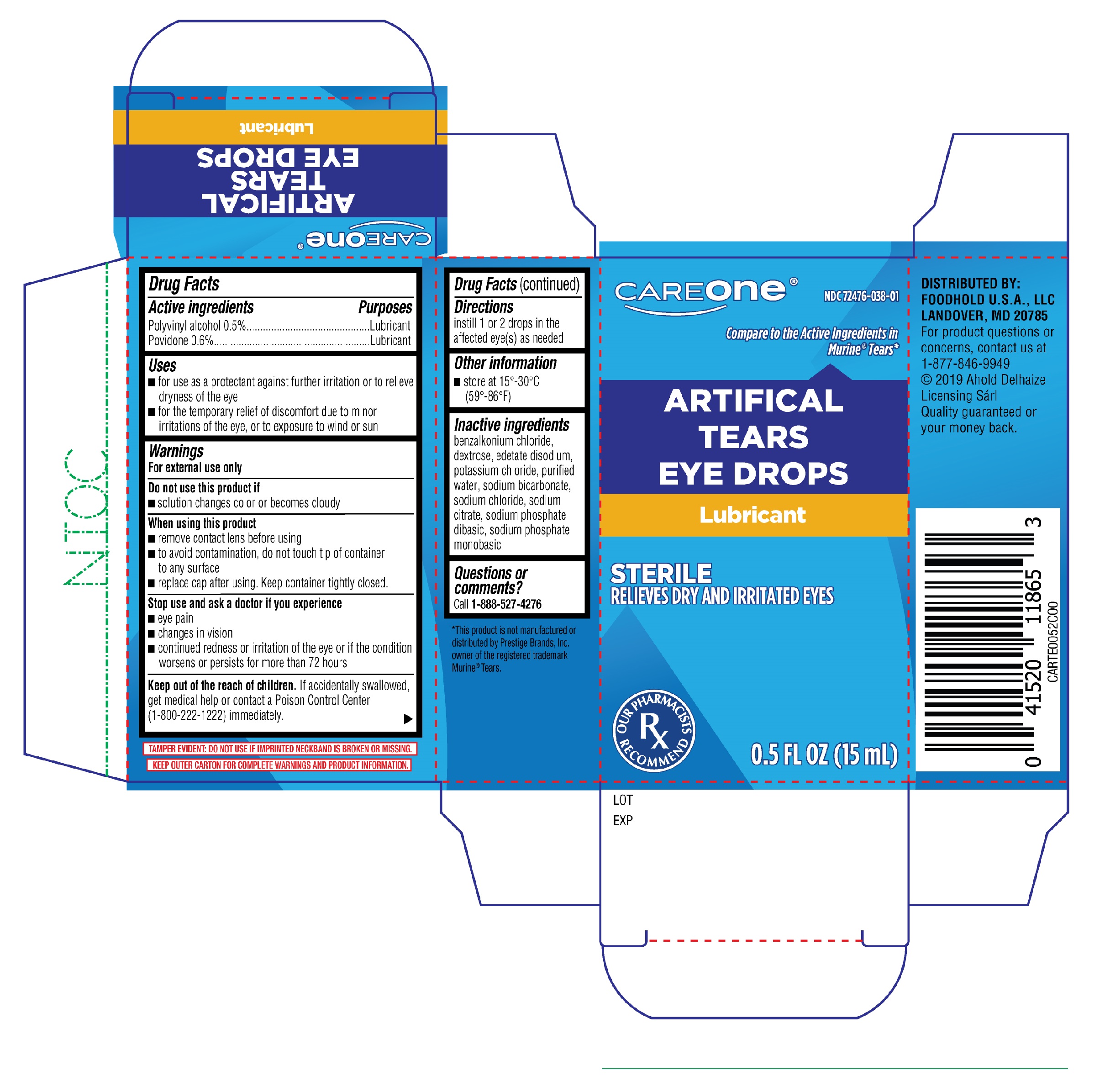 DRUG LABEL: CareOne Artificial Tears Eye Drops 15mL
NDC: 72476-038 | Form: SOLUTION/ DROPS
Manufacturer: Retail Business Services, LLC
Category: otc | Type: HUMAN OTC DRUG LABEL
Date: 20251230

ACTIVE INGREDIENTS: POLYVINYL ALCOHOL, UNSPECIFIED 0.5 g/100 mL; POVIDONE 0.6 g/100 mL
INACTIVE INGREDIENTS: BENZALKONIUM CHLORIDE; EDETATE DISODIUM; WATER; SODIUM BICARBONATE; SODIUM CITRATE; SODIUM PHOSPHATE, DIBASIC, ANHYDROUS; SODIUM PHOSPHATE, MONOBASIC, ANHYDROUS; DEXTROSE; POTASSIUM CHLORIDE; SODIUM CHLORIDE

CareOne Artificial Tears Eye Drops 15mL (PLD)

Active Ingredients

Polyvinyl Alcohol 0.5%

Povidone 0.6%

Purposes

Lubricant

Lubricant

Uses

- for use as a protectant against further irritation or to relieve dryness of the eye
- for the temporary relief of discomfort due to minor irritations of the eye, or exposure to wind or sun

Warnings

For external use only

When using this product

- remove contact lens before using
- to avoid contamination, do not touch tip of container to any surface
- replace cap after using. Keep container tightly closed.

Do not use this product if

- solution changes color or becomes cloudy

Stop use and ask a doctor if you experience

- eye pain
- changes in vision
- continued redness or irritation of the eye or if the condition worsens or persists for more than 72 hours

Keep out of the reach of children.

if accidentally swallowed, get medical help or contact a Poison Control Center (1-800-222-1222) immediately.

Directions

instill 1 or 2 drops in the affected eye(s) as needed

Other information

- store at 15°-30°C (59°-86°F)

Inactive ingredients

benzalkonium chloride, dextrose, edetate disodium, potassium chloride, purified water, sodium bicarbonate, sodium chloride, sodium citrate, sodium phosphate dibasic, sodium phosphate monobasic

Questions or comments?

Call 1-888-527-4276